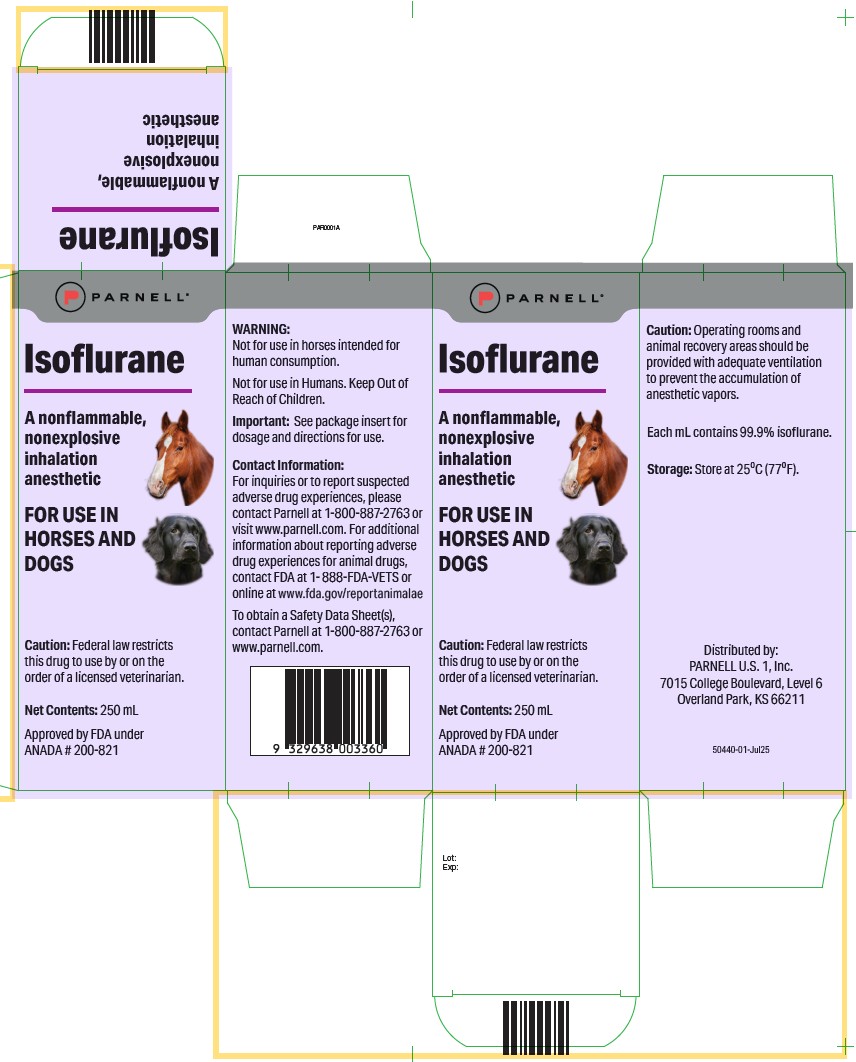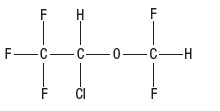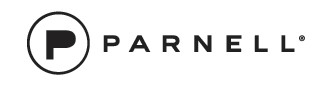 DRUG LABEL: Isoflurane
NDC: 68504-010 | Form: LIQUID
Manufacturer: Parnell Technologies Pty Ltd
Category: animal | Type: PRESCRIPTION ANIMAL DRUG LABEL
Date: 20251030

ACTIVE INGREDIENTS: Isoflurane 99.9 mL/100 mL

Isoflurane
Inhalation Anesthetic
For Use in Horses and Dogs

WARNING

Not for use in horses intended for human consumption.
Not for use in Humans. Keep Out of Reach of Children.

CAUTION
Federal law restricts this drug to use by or on the order of a licensed veterinarian.

DESCRIPTION

Isoflurane is a nonflammable, nonexplosive general inhalation anesthetic agent. Its chemical name is 1-chloro-2,2,2-trifluoroethyl difluoromethyl ether, and its structural formula is:

Each mL contains 99.9% isoflurane.

Some physical constants are:

Some physical constants are:
Molecular weight ............................................... 184.5
Boiling point at 760 mm Hg ................................ 48.5°C (uncorr.)
Refractive index n20D ....................................... 1.2990-1.3005
Specific gravity 25°/25°C .................................. 1.496
Vapor pressure in mm Hg** ......................................
20°C 238
25°C 295
30°C 367
35°C 450

**Equation for vapor pressure calculation: log10 Pv = A + B/(T + C)
A = 8.056
B = -1664.58
T = °C + 273.16 (Kelvin)

Partition coefficients at 37°C:
Water/gas .................................................... 0.61
Blood/gas .................................................... 1.43
Oil/gas ........................................................ 90.8

Partition coefficients at 25°C – rubber and plastic:
Conductive rubber/gas ....................................... 62.0
Butyl rubber/gas ............................................... 75.0
Polyvinyl chloride/gas ...................................... 110.0
Polyethylene/gas ............................................. ~2.0
Polyurethane/gas ............................................. ~1.4
Polyolefin/gas .................................................. ~1.1
Butyl acetate/gas ............................................. ~2.5
Purity by gas chromatography ........................ >99.9%

Lower limit of flammability in oxygen or nitrous oxide at 9 joules/sec and 23°C .................. None

Lower limit of flammability in oxygen or nitrous oxide at 900 joules/sec and 23°C ........ Greater than useful concentrations in anesthesia

MAC (Minimum Alveolar Concentration) is 1.31% in horses¹ and 1.28% in dogs.⁶.

Isoflurane is a clear, colorless, stable liquid containing no additives or chemical stabilizers. Isoflurane has a mildly pungent, musty, etheral odor. Samples stored in indirect sunlight in clear, colorless glass for five years, as well as samples directly exposed for 30 hours to a 24,000 ft. candle tungsten light, showed no change in composition as determined by gas chromatography. Isoflurane in one normal sodium methoxide-methanol solution, a strong base, for two months contained essentially no alkali, indicative of strong base stability. Isoflurane does not decompose in the presence of soda lime (at normal operating temperatures), and does not attack aluminum, tin, brass, iron, or copper.

CLINICAL PHARMACOLOGY

Isoflurane is an inhalation anesthetic. Induction and recovery from anesthesia with isoflurane are rapid.²⁵ The level of anesthesia may be changed rapidly with isoflurane. Isoflurane is a profound respiratory depressant. RESPIRATION MUST BE MONITORED CLOSELY IN THE HORSE AND DOG AND SUPPORTED WHEN NECESSARY. As anesthetic dose is increased, both tidal volume and respiratory rate decrease.³⁶ This depression is partially reversed by surgical stimulation, even at deeper levels of anesthesia.

Blood pressure decreases with induction of anesthesia but returns toward normal with surgical stimulation. Progressive increases in depth of anesthesia produce corresponding decreases in blood pressure; however, heart rhythm is stable and cardiac output is maintained with controlled ventilation and normal PaCO₂ despite increasing depth of anesthesia. The hypercapnia which attends spontaneous ventilation during isoflurane anesthesia increases heart rate and raises cardiac output above levels observed with controlled ventilation.³ Isoflurane does not sensitize the myocardium to exogenously administered epinephrine in the dog.

Muscle relaxation may be adequate for intra-abdominal operations at normal levels of anesthesia. However, if muscle relaxants are used to achieve greater relaxation, it should be noted that: ALL COMMONLY USED MUSCLE RELAXANTS ARE MARKEDLY POTENTIATED WITH ISOFLURANE, THE EFFECT BEING MOST PROFOUND WITH THE NONDEPOLARIZING TYPE. Neostigmine reverses the effect of nondepolarizing muscle relaxants in the presence of isoflurane but does not reverse the direct neuromuscular depression of isoflurane.

CONTRAINDICATIONS

Isoflurane is used for induction and maintenance of general anesthesia in horses and dogs.

CONTRAINDICATIONS

Isoflurane is contraindicated in horses and dogs with known sensitivity to isoflurane or to other halogenated agents.

WARNINGS

Increasing depth of anesthesia with Isoflurane may increase hypotension and respiratory depression. The electroencephalographic pattern associated with deep anesthesia is characterized by burst suppression, spiking, and isoelectric periods⁴.

Since levels of anesthesia may be altered easily and rapidly, only vaporizers producing predictable percentage concentrations of isoflurane should be used (see DOSAGE AND ADMINISTRATION).

The action of nondepolarizing relaxants is augmented by isoflurane. Less than the usual amounts of these drugs should be used. If the usual amounts of nondepolarizing relaxants are given, the time for recovery from myoneural blockade will be longer in the presence of isoflurane than in the presence of other commonly used anesthetics.

Not for use in horses intended for human consumption.

Not for use in Humans. Keep Out of Reach of Children.

PRECAUTIONS

Isoflurane, like some other inhalational anesthetics, can react with desiccated carbon dioxide (CO₂) absorbents to produce carbon monoxide which may result in elevated carboxyhemoglobin levels in some patients. Case reports suggest that barium hydroxide lime and soda lime become desiccated when fresh gases are passed through the CO₂ absorber canister at high flow rates over many hours or days. When a clinician suspects that CO₂ absorbent may be desiccated, it should be replaced before the administration of isoflurane.

Usage in Pregnancy: Reproduction studies have been performed in mice and rats with no evidence of fetal malformation attributable to isoflurane. Adequate data concerning the safe use of isoflurane in pregnant and breeding horses and dogs have not been obtained.

ADVERSE REACTIONS

Hypotension, respiratory depression and arrhythmias have been reported.

OVERDOSAGE

In the event of overdosage, or what may appear to be overdosage, the following action should be taken:

Stop drug administration, establish that the airway is clear and initiate assisted or controlled ventilation with pure oxygen as circumstances dictate.

DOSAGE AND ADMINISTRATION

Caution: Operating rooms and animal recovery areas should be provided with adequate ventilation to prevent accumulation of anesthetic vapors.

Premedication: A premedication regimen, which may be employed depending upon the patient status, to avert excitement during induction, might include an anticholinergic, a tranquilizer, a muscle relaxant, and a short-acting barbiturate.

Inspired Concentration: The delivered concentration of Isoflurane should be known. Isoflurane may be vaporized using a flow-through vaporizer specifically calibrated for isoflurane. Vaporizers delivering a saturated vapor which then is diluted (e.g., Vernitrol® vaporizer) also may be used. The delivered concentration from such a vaporizer may be calculated using the formula:

% isoflurane = 100P₍ᵥ₎F₍ᵥ₎
──────────────
F₍ₜ₎(P₍ₐ₎ - P₍ᵥ₎)

Where: Pₐ = Pressure of atmosphere
Pᵥ = Vapor pressure of isoflurane
Fᵥ = Flow of gas through vaporizer (mL/min)
Fₜ = Total gas flow used (mL/min)

Isoflurane contains no stabilizer. Nothing in the drug product alters calibration or operation of these vaporizers.

Induction

Horses: Inspired concentrations of 3.0 to 5.0% isoflurane alone with oxygen following a barbiturate anesthetic induction are usually employed to induce surgical anesthesia in the horse.

Dogs: Inspired concentrations of 2.0 to 2.5% isoflurane alone with oxygen following a barbiturate anesthetic induction are usually employed to induce surgical anesthesia in the dog.

These concentrations can be expected to produce surgical anesthesia in 5 to 10 minutes.

Maintenance:
The concentration of vapor necessary to maintain anesthesia is much less than that required to induce it.

Horses: Surgical levels of anesthesia in the horse may be sustained with a 1.5 to 1.8% concentration of isoflurane in oxygen.

Dogs: Surgical levels of anesthesia in the dog may be sustained with a 1.5 to 1.8% concentration of isoflurane in oxygen.

The level of blood pressure during maintenance is an inverse function of isoflurane concentration in the absence of other complicating problems. Excessive decreases, unless related to hypovolemia, may be due to depth of anesthesia and in such instances may be corrected by lightening the level of anesthesia.

Recovery from isoflurane anesthesia is typically uneventful.²

HOW SUPPLIED

Isoflurane is supplied in 250 mL amber-colored bottles.

250 mL bottle package of one

Storage: Store at room temperature 25°C (77° F).

CONTACT INFORMATION

For inquiries or to report suspected adverse drug experiences, please contact Parnell at 1-800-887-2763 or visit www.parnell.com. For additional information about reporting adverse drug experiences for animal drugs, contact FDA at 1- 888-FDA-VETS or online at www.fda.gov/reportanimalae

To obtain a Safety Data Sheet(s), contact Parnell at 1-800-887-2763 or www.parnell.com.

REFERENCES

1. Steffey, E. P., Howland, D. Jr., Giri, S. and Eger, E.I.II. Enflurane, Halothane and Isoflurane Potency in Horses. Am. J. Vet. Res. 1977; 38(7): 1037-1039.
2. Auer, J. A., Garner, H.E., Amend, J.F., Hutcheson, D.P. and Salem, C.A. Recovery from Anesthesia in Ponies: A Comparative Study of the Effects of Isoflurane, Enflurane, Methoxyflurane and Halothane. Equine Vet J. 1978; 10(1): 18-23.
3. Steffey, E.P., and Howland, D. Jr. Comparison of Circulatory and Respiratory Effects of Isoflurane and Halothane Anesthesia in Horses. Am. J. Vet. Res. 1980; 41(5): 821-825.
4. Auer, J.A., Amend, J.F., Garner, H.E., Hutcheson, D.P. and Salem, C.A. Electroencephalographic Responses During Volatile Anesthesia in Domestic Ponies: A Comparative Study of Isoflurane, Enflurane, Methoxyflurane, and Halothane. Equine Practice 1979; 3: 130-134.
5. Klide, A.M. Cardiopulmonary Effects of Enflurane and Isoflurane in the Dog. Am. J. Vet. Res. 1976; Vol. 37, No. 2: 127-131.
6. Steffey, E. P., Howland, D. Jr. Isoflurane Potency in the Dog and Cat. Am. J. Vet. Res. 1977; Vol. 38, No. 11: 1833-1836.

Approved by FDA under ANADA # 200-821

Distributed by: PARNELL U.S. 1, Inc.
7015 College Boulevard, Level 6,
Overland Park, KS, 66211

50441-01-Jul25

Principal Display Panel – 250 mL Carton

Isoflurane

A nonflammable, nonexplosive inhalation anesthetic

FOR USE IN HORSES AND DOGS

Caution: Federal law restricts this drug to use by or on the order of a licensed veterinarian.

Net Contents: 250 mL

Approved by FDA under ANADA # 200-821